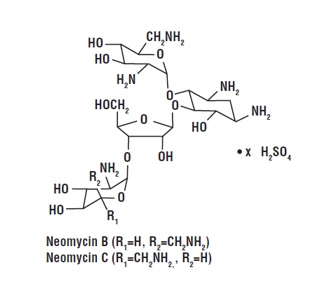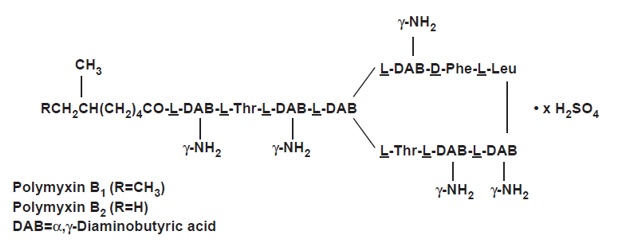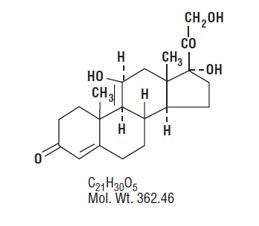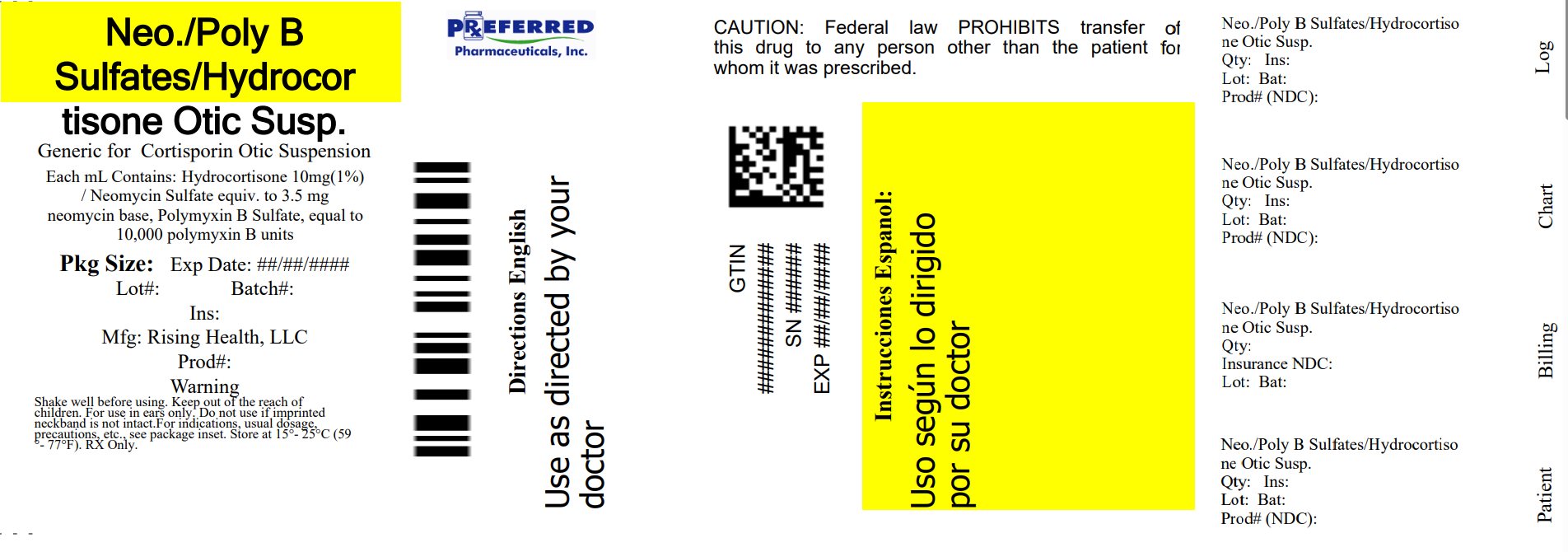 DRUG LABEL: Neomycin and Polymyxin B Sulfates and Hydrocortisone Otic Suspension
NDC: 68788-7787 | Form: SUSPENSION
Manufacturer: Preferred Pharmaceuticals, Inc.
Category: prescription | Type: HUMAN PRESCRIPTION DRUG LABEL
Date: 20250819

ACTIVE INGREDIENTS: HYDROCORTISONE 10 mg/1 mL; NEOMYCIN SULFATE 3.5 mg/1 mL; POLYMYXIN B SULFATE 10000 [USP'U]/1 mL
INACTIVE INGREDIENTS: CETYL ALCOHOL; POLYSORBATE 80; PROPYLENE GLYCOL; WATER; SULFURIC ACID; THIMEROSAL

Neomycin and Polymyxin B Sulfates and Hydrocortisone Otic Suspension, USP
Sterile

DESCRIPTION

Neomycin and Polymyxin B Sulfates and Hydrocortisone Otic Suspension, USP is a sterile antibacterial and anti-inflammatory suspension for otic use. Each mL contains: neomycin sulfate equivalent to 3.5 mg neomycin base, polymyxin B sulfate equivalent to 10,000 polymyxin B units, and hydrocortisone 10 mg (1%). The vehicle contains thimerosal 0.01% (added as a preservative) and the inactive ingredients cetyl alcohol, propylene glycol, polysorbate 80, and Water for Injection. Sulfuric acid may be added to adjust pH.

Neomycin sulfate is the sulfate salt of neomycin B and C, which are produced by the growth of Streptomyces fradiae Waksman (Fam. Streptomycetaceae). It has a potency equivalent of not less than 600 mcg of neomycin standard per mg, calculated on an anhydrous basis. The structural formulae are:

Polymyxin B sulfate is the sulfate salt of polymyxin B1 and B2, which are produced by the growth of Bacillus polymyxa (Prazmowski) Migula (Fam. Bacillaceae). It has a potency of not less than 6,000 polymyxin B units per mg, calculated on an anhydrous basis. The structural formulae are:

Hydrocortisone, 11β, 17, 21-trihydroxypregn-4-ene-3, 20-dione, is an anti-inflammatory hormone. Its structural formula is:

CLINICAL PHARMACOLOGY

Corticoids suppress the inflammatory response to a variety of agents and they may delay healing. Since corticoids may inhibit the body's defense mechanism against infection, a concomitant antimicrobial drug may be used when this inhibition is considered to be clinically significant in a particular case.

The anti-infective components in the combination are included to provide action against specific organisms susceptible to them. Neomycin sulfate and polymyxin B sulfate together are considered active against the following microorganisms: Staphylococcus aureus, Escherichia coli, Haemophilus influenzae, Klebsiella-Enterobacter species, Neisseria species, and Pseudomonas aeruginosa. This product does not provide adequate coverage against Serratia marcescens and streptococci, including Streptococcus pneumoniae.

The relative potency of corticosteroids depends on the molecular structure, concentration, and release from the vehicle.

INDICATIONS AND USAGE

For the treatment of superficial bacterial infections of the external auditory canal caused by organisms susceptible to the action of the antibiotics, and for the treatment of infections of mastoidectomy and fenestration cavities caused by organisms susceptible to the antibiotics.

CONTRAINDICATIONS

This product is contraindicated in those individuals who have shown hypersensitivity to any of its components, and in herpes simplex, vaccinia, and varicella infections.

WARNINGS

Neomycin can induce permanent sensorineural hearing loss due to cochlear damage, mainly destruction of hair cells in the organ of Corti. The risk is greater with prolonged use. Therapy should be limited to 10 consecutive days (see). Patients being treated with eardrops containing neomycin should be under close clinical observation. Neomycin and Polymyxin B Sulfates and Hydrocortisone Otic Suspension should not be used in any patient with a perforated tympanic membrane.

Discontinue promptly if sensitization or irritation occurs.

Neomycin sulfate may cause cutaneous sensitization. A precise incidence of hypersensitivity reactions (primarily skin rash) due to topical neomycin is not known.

When using neomycin-containing products to control secondary infection in the chronic dermatoses, such as chronic otitis externa or stasis dermatitis, it should be borne in mind that the skin in these conditions is more liable than is normal skin to become sensitized to many substances, including neomycin. The manifestation of sensitization to neomycin is usually a low-grade reddening with swelling, dry scaling, and itching; it may be manifest simply as a failure to heal. Periodic examination for such signs is advisable, and the patient should be told to discontinue the product if they are observed. These symptoms regress quickly on withdrawing the medication. Neomycin containing applications should be avoided for the patient thereafter.

PRECAUTIONS

General:

As with other antibiotic preparations, prolonged use may result in overgrowth of nonsusceptible organisms, including fungi.

If the infection is not improved after 1 week, cultures and susceptibility tests should be repeated to verify the identity of the organism and to determine whether therapy should be changed.

Treatment should not be continued for longer than 10 days.

Allergic cross-reactions may occur which could prevent the use of any or all of the following antibiotics for the treatment of future infections: kanamycin, paromomycin, streptomycin, and possibly gentamicin.

Information for Patients:

Avoid contaminating the bottle tip with material from the ear, fingers, or other source. This caution is necessary if the sterility of the drops is to be preserved.

If sensitization or irritation occurs, discontinue use immediately and contact your physician.

SHAKE WELL BEFORE USING.

Carcinogenesis, Mutagenesis, Impairment of Fertility:

Long-term studies in animals (rats, rabbits, mice) showed no evidence of carcinogenicity attributable to oral administration of corticosteroids.

Pregnancy

Teratogenic Effects:

Corticosteroids have been shown to be teratogenic in rabbits when applied topically at concentrations of 0.5% on days 6 to 18 of gestation and in mice when applied topically at a concentration of 15% on days 10 to 13 of gestation. There are no adequate and well-controlled studies in pregnant women. Corticosteroids should be used during pregnancy only if the potential benefit justifies the potential risk to the fetus.

Nursing Mothers:

Hydrocortisone appears in human milk following oral administration of the drug. Since systemic absorption of hydrocortisone may occur when applied topically, caution should be exercised when neomycin and polymyxin B sulfates and hydrocortisone otic suspension is used by a nursing woman.

Pediatric Use:

The safety and effectiveness of neomycin and polymyxin B sulfates and hydrocortisone otic suspension in otitis externa have been established in pediatric patients.

Geriatric Use:

Clinical studies of neomycin and polymyxin B sulfates and hydrocortisone otic suspension did not include sufficient numbers of subjects aged 65 and over to determine whether they respond differently from younger subjects. Other reported clinical experience has not identified differences in responses between the elderly and younger patients.

ADVERSE REACTIONS

Neomycin occasionally causes skin sensitization. Ototoxicity and nephrotoxicity have also been reported (see). Adverse reactions have occurred with topical use of antibiotic combinations including neomycin and polymyxin B. Exact incidence figures are not available since no denominator of treated patients is available. The reaction occurring most often is allergic sensitization.

The following local adverse reactions have been reported with topical corticosteroids, especially under occlusive dressings: burning, itching, irritation, dryness, folliculitis, hypertrichosis, acneiform eruptions, hypopigmentation, perioral dermatitis, allergic contact dermatitis, maceration of the skin, secondary infection, skin atrophy, striae and miliaria. Stinging and burning have been reported rarely when this drug has gained access to the middle ear.

To report SUSPECTED ADVERSE REACTIONS, contact Rising Pharma Holdings, Inc. at 1-844-874-7464 or FDA at 1-800-FDA-1088 or www.fda.gov/medwatch.

DOSAGE AND ADMINISTRATION

Therapy with this product should be limited to 10 consecutive days. The external auditory canal should be thoroughly cleansed and dried with a sterile cotton applicator.

For adults, 4 drops of the suspension should be instilled into the affected ear 3 or 4 times daily.

For children, 3 drops are suggested because of the smaller capacity of the ear canal.

The patient should lie with the affected ear upward and then the drops should be instilled. This position should be maintained for 5 minutes to facilitate penetration of the drops into the ear canal. Repeat, if necessary, for the opposite ear.

If preferred, a cotton wick may be inserted into the canal and then the cotton may be saturated with the suspension. This wick should be kept moist by adding further suspension every 4 hours. The wick should be replaced at least once every 24 hours.

SHAKE WELL BEFORE USING.

HOW SUPPLIED

10 mL bottle (NDC 68788-7787-1). Store at 15° to 25°C (59° to 77°F).

Rx only

KEEP OUT OF REACH OF CHILDREN.

Distributed by:
Rising Pharma Holdings, Inc.
East Brunswick, NJ 08816

Code No.: TS/DRUGS/13/2010

Made in India

PIA44801-03
Revised: 05/2024

P1537072

Principal Display Panel

Neomycin and Polymyxin B Sulfates and Hydrocortisone Otic Suspension, USP
Sterile
FOR USE IN EARS.
10 mL
NDC (NDC 68788-7787-1).

Carton label

Neomycin and Polymyxin B Sulfates and Hydrocortisone Otic Suspension, USP
Sterile

FOR USE IN EARS.

10 mL

NDC (NDC 68788-7787-1).

Container label